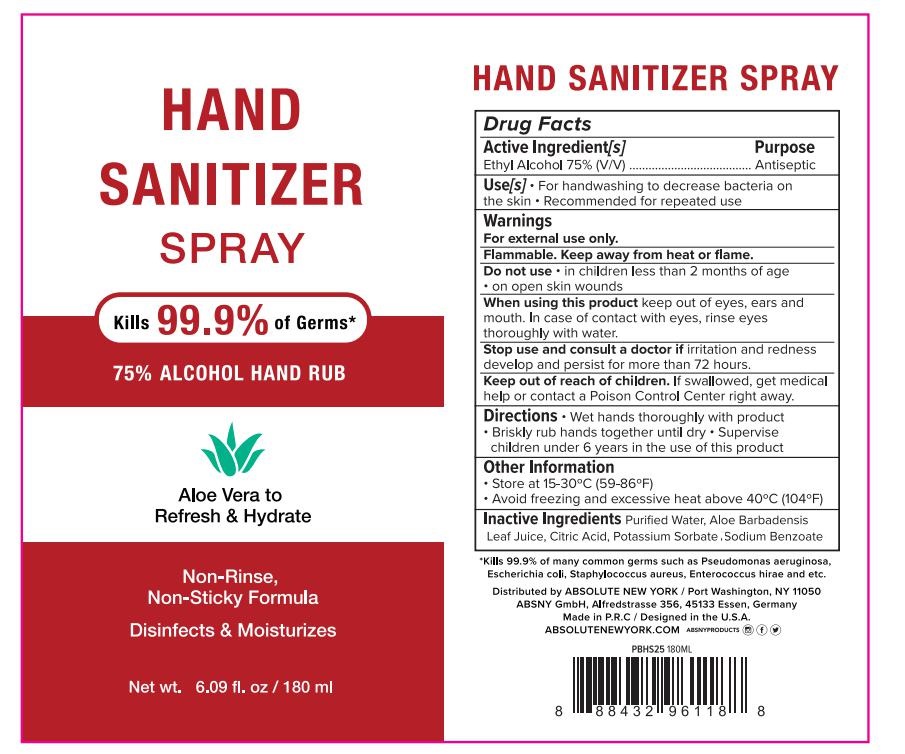 DRUG LABEL: HAND SANITIZER
NDC: 74765-016 | Form: SPRAY
Manufacturer: Zhejiang Yiwu Limei Cosmetics Co.,Ltd
Category: otc | Type: HUMAN OTC DRUG LABEL
Date: 20200530

ACTIVE INGREDIENTS: ALCOHOL 75 mL/100 mL
INACTIVE INGREDIENTS: ALOE VERA LEAF; ANHYDROUS CITRIC ACID; WATER; SODIUM BENZOATE; POTASSIUM SORBATE

NA

Active Ingredient(s)

Ethyl Alcohol 75% v/v. Purpose: Antiseptic

Purpose

Antiseptic, Hand Sanitizer

Use

For handwashing to decrease bacteria on the skin. Recommended for repeated use.

Warnings

For external use only. Flammable. Keep away from heat or flame

Do not use

- in children less than 2 months of age
- on open skin wounds

When using this product keep out of eyes, ears, and mouth. In case of contact with eyes, rinse eyes thoroughly with water.
Stop use and ask a doctor if irritation and redness develop and persist for more than 72 hours.
Keep out of reach of children. If swallowed, get medical help or contact a Poison Control Center right away.

Stop use and ask a doctor if irritation and redness develop and persist for more than 72 hours.

Keep out of reach of children. If swallowed, get medical help or contact a Poison Control Center right away.

Directions

- wet hands thoroughly with product.
- briskly rub hands together until dry.
- supervise children under 6 years in the use of this product.

Other information

- Store between 15-30C (59-86F)
- Avoid freezing and excessive heat above 40C (104F)

Inactive ingredients

purified water, Aloe Barbadensis Leaf Juice, Citric Acid, Potassium Sorbate, Sodium Benzoate

Package Label - Principal Display Panel

100 mL NDC: 74765-016-01

180 mL NDC: 74765-016-02